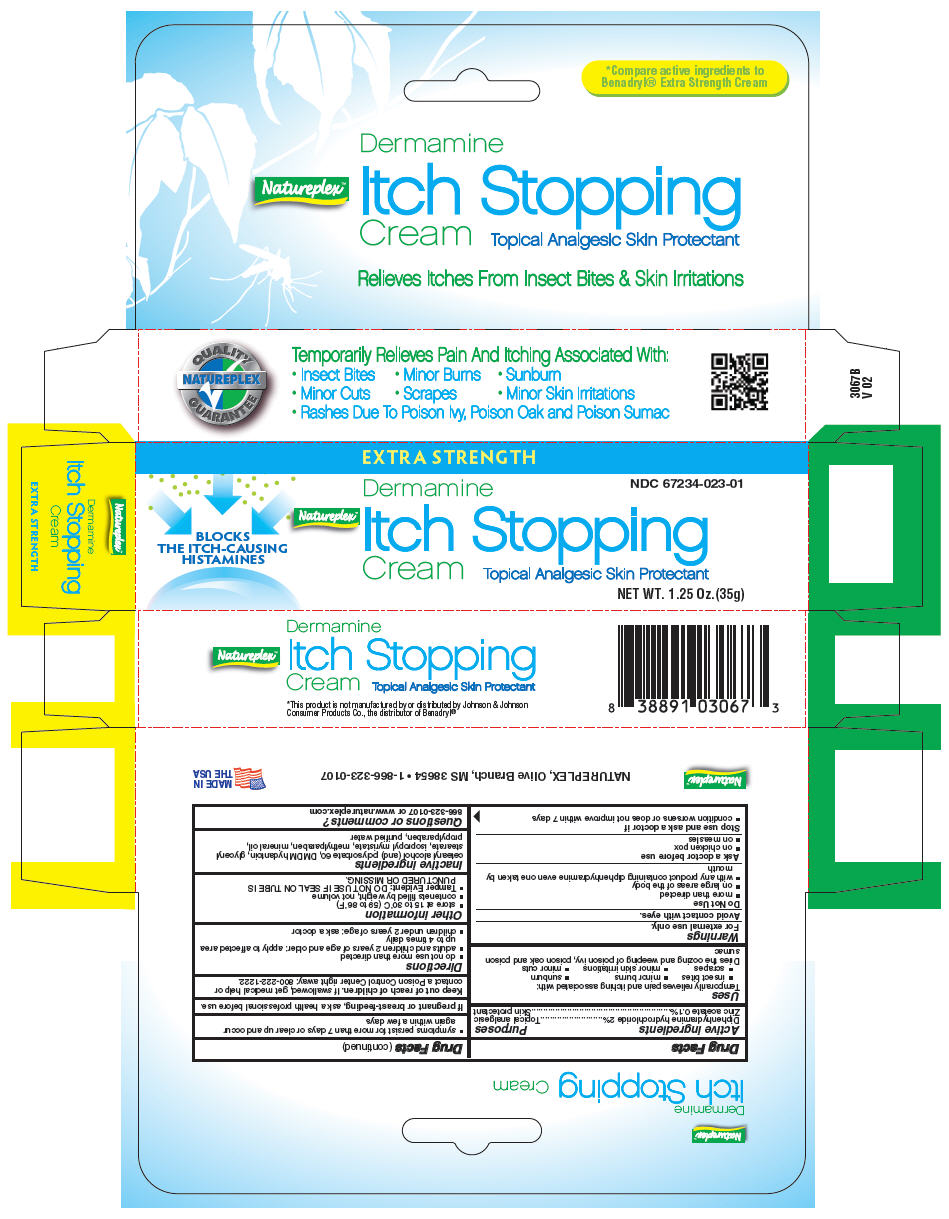 DRUG LABEL: Dermamine 
NDC: 67234-023 | Form: CREAM
Manufacturer: Natureplex LLC
Category: otc | Type: HUMAN OTC DRUG LABEL
Date: 20241231

ACTIVE INGREDIENTS: DIPHENHYDRAMINE 0.02 mg/1 g; ZINC ACETATE 0.001 U/1 g
INACTIVE INGREDIENTS: DMDM HYDANTOIN; GLYCERYL 1-STEARATE; ISOPROPYL MYRISTATE; LIGHT MINERAL OIL; METHYLPARABEN; PROPYLPARABEN; CETOSTEARYL ALCOHOL; POLYSORBATE 60; WATER

Dermamine
Extra Strength Itch Stopping Cream

Drug Facts

ACTIVE INGREDIENT

PURPOSE

Active ingredients | Purposes
Diphenhydramine Hydrochloride 2% | Topical Analgesic
Zinc Acetate 0.1% | Skin Protectant

Uses

- Temporarily relieves pain and itching associated with:
  - insect bites
  - minor burns
  - sunburn
  - scrapes
  - minor skin irritations
  - minor cuts
  - rashes due to poison ivy, poison oak and poison sumac
- dries the oozing and weeping of poison ivy, poison oak and poison sumac

Warnings

For external use only

Do not use

- on large areas of the body
- with any other product containing diphenhydramine, even one taken by mouth

Ask a doctor before use

- on chicken pox
- on measles

When using this product avoid contact with eyes

Stop use and ask a doctor if

- condition worsens or does not improve within 7 days
- symptoms persist for more than 7 days or clear up and occur again within a few days

KEEP OUT OF REACH OF CHILDREN

Keep out of the reach of children. In case of accidental ingestion, seek medical attention right away or contact a Poison Control Center immediately.

Directions

- do not use more than directed
- adults and children 2 years of age and older: apply to affected area not more than 3 to 4 times daily
- children under 2 years of age: ask a doctor

Other information

- store between 15° and 30° C (59° and 86° F)
- close cap tightly after use
- do not use if seal on tube is punctured or missing

Inactive ingredients

DMDM Hydantoin, GMS, isopropyl myristate, light mineral oil, methylparaben, propylparaben, ritacol, purified water

Questions or comments?

1-866-323-0107

PRINCIPAL DISPLAY PANEL - 35 g Tube Box

EXTRA STRENGTH

BLOCKS
THE ITCH-CAUSING
HISTAMINES

Natureplex™

Dermamine
Itch Stopping
Cream
Topical Analgesic Skin Protectant

NDC 67234-023-01

NET WT. 1.25 Oz.(35g)